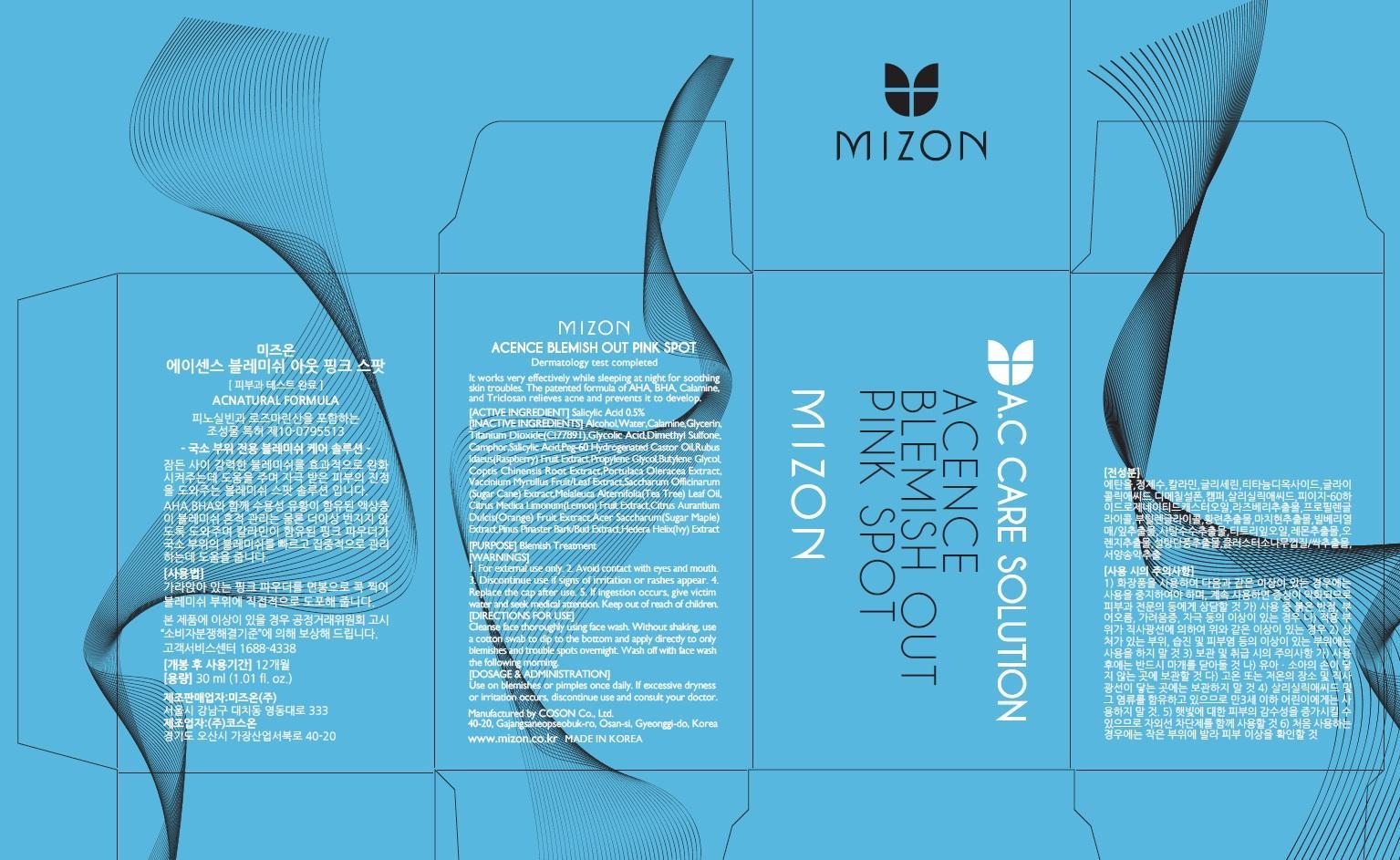 DRUG LABEL: MIZON ACENCE BLEMISH OUT PINK SPOT
NDC: 57718-060 | Form: SOLUTION
Manufacturer: MIZON CO., LTD.
Category: otc | Type: HUMAN OTC DRUG LABEL
Date: 20150825

ACTIVE INGREDIENTS: Salicylic Acid 0.15 mg/30 mL
INACTIVE INGREDIENTS: Alcohol; Water

ACTIVE INGREDIENT

Active Ingredient: Salicylic Acid 0.5%

INACTIVE INGREDIENT

Inactive Ingredients: Alcohol, Water, Calamine, Glycerin, Titanium Dioxide(CI77891), Glycolic Acid, Dimethyl Sulfone, Camphor, Peg-60 Hydrogenated Castor Oil, Rubus Idaeus(Raspberry) Fruit Extract, Propylene Glycol, Butylene Glycol, Coptis Chinensis Root Extract, Portulaca Oleracea Extract, Vaccinium Myrtillus Fruit/Leaf Extract, Saccharum Officinarum(Sugar Cane) Extract, Melaleuca Alternifolia(Tea Tree) Leaf Oil, Citrus Medica Limonum(Lemon) Fruit Extract, Citrus Aurantium Dulcis(Orange) Fruit Extract, Acer Saccharum(Sugar Maple) Extract, Pinus Pinaster Bark/Bud Extract, Hedera Helix(Ivy) Extract, Citrus Grandis(Grapefruit) Peel Oil

PURPOSE

Purpose: Blemish Treatment

WARNINGS

Warnings: 1. For external use only. 2. Avoid contact with eyes and mouth. 3. Discontinue use if signs of irritation or rashes appear. 4. Replace the cap after use. 5. If ingestion occurs, give victim water and seek medical attention.

KEEP OUT OF REACH OF CHILDREN

Directions for use: Cleanse face thoroughly using face wash. Without shaking, use a cotton swab to dip to the bottom and apply directly to only blemishes and trouble spots overnight. Wash off with face wash the following morning.

DOSAGE & ADMINISTRATION

Dosage & Administration: Use on blemishes or pimples once daily. If excessive dryness or irritation occurs, discontinue use and consult your doctor.